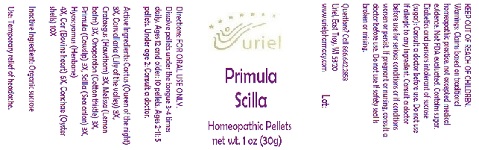 DRUG LABEL: Primula Scilla
NDC: 48951-8068 | Form: PELLET
Manufacturer: Uriel Pharmacy Inc.
Category: homeopathic | Type: HUMAN OTC DRUG LABEL
Date: 20180606

ACTIVE INGREDIENTS: SELENICEREUS GRANDIFLORUS STEM 3 [hp_X]/1 1; CONVALLARIA MAJALIS 3 [hp_X]/1 1; HAWTHORN LEAF WITH FLOWER 3 [hp_X]/1 1; MELISSA OFFICINALIS 3 [hp_X]/1 1; ONOPORDUM ACANTHIUM FLOWER 3 [hp_X]/1 1; PRIMULA VERIS FLOWER 3 [hp_X]/1 1; DRIMIA MARITIMA BULB 3 [hp_X]/1 1; HYOSCYAMUS NIGER LEAF 4 [hp_X]/1 1; BEEF HEART 6 [hp_X]/1 1; OSTREA EDULIS SHELL 10 [hp_X]/1 1
INACTIVE INGREDIENTS: SUCROSE

Primula Scilla

INDICATIONS AND USAGE

Directions: FOR ORAL USE ONLY.

DOSAGE AND ADMINISTRATION

Dissolve pellets under the tongue 3-4 times daily. Ages 12 and older: 10 pellets. Ages 2-11: 5 pellets. Under age 2: Consult a doctor.

ACTIVE INGREDIENT

Active Ingredients: Cactus (Queen of the night) 3X, Convallaria (Lily of the valley) 3X, Crataegus (Hawthorn) 3X, Melissa (Lemon balm) 3X, Onopordon (Cotton thistle) 3X, Primula (Cowslip) 3X, Scilla (Sea onion) 3X, Hyoscyamus (Henbane)
4X, Cor (Bovine heart) 6X, Conchae (Oyster shells) 10X

Inactive Ingredient: Organic sucrose

PURPOSE

Use: Temporary relief of headache.

KEEP OUT OF REACH OF CHILDREN.

WARNINGS

Warnings: Claims based on traditional homeopathic practice, not accepted medical evidence. Not FDA evaluated. Contains sugar. Diabetics and persons intolerant of sucrose (sugar): Consult a doctor before use. Do not use if allergic to any ingredient. Consult a doctor before use for serious conditions or if conditions worsen or persist. If pregnant or nursing, consult a doctor before use. Do not use if safety seal is broken or missing.

QUESTIONS

Questions? Call 866.642.2858 Uriel, East Troy, WI 53120 www.urielpharmacy.com